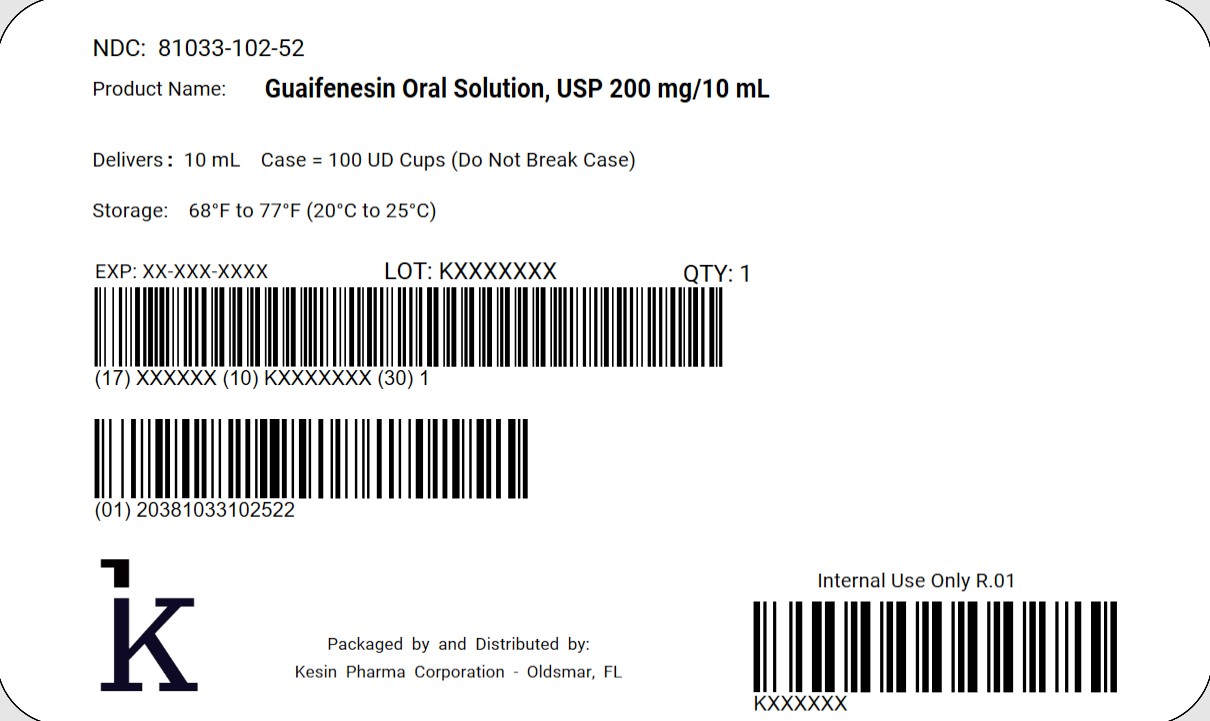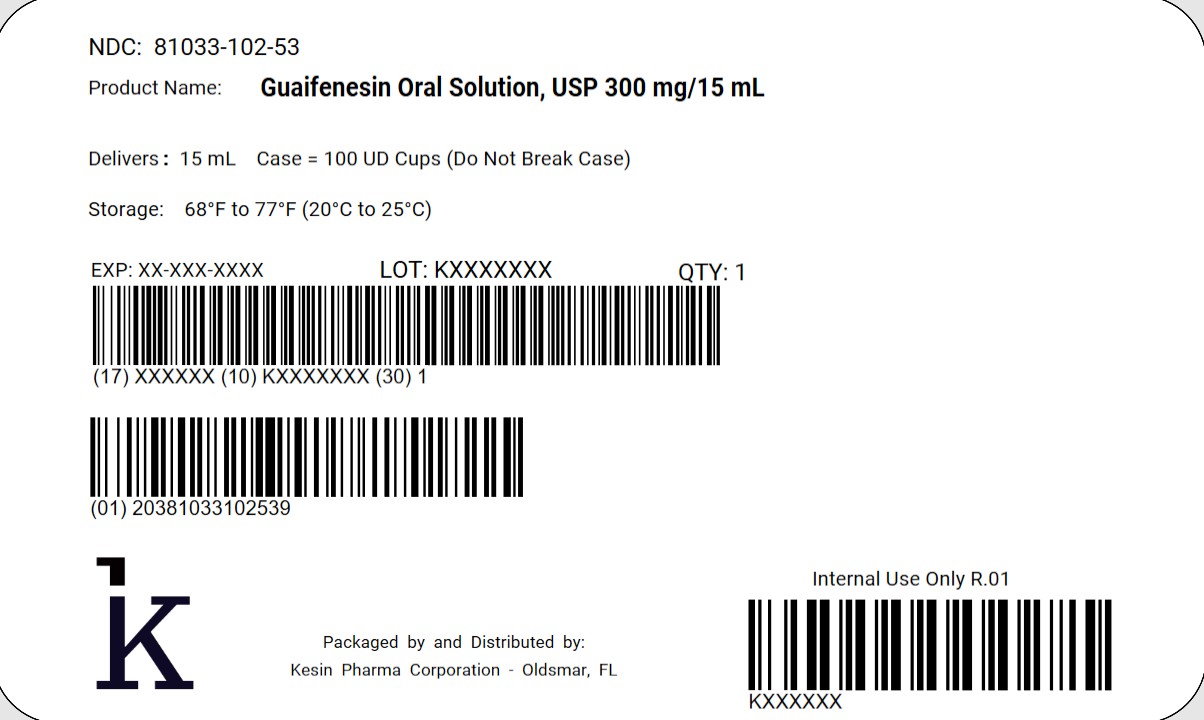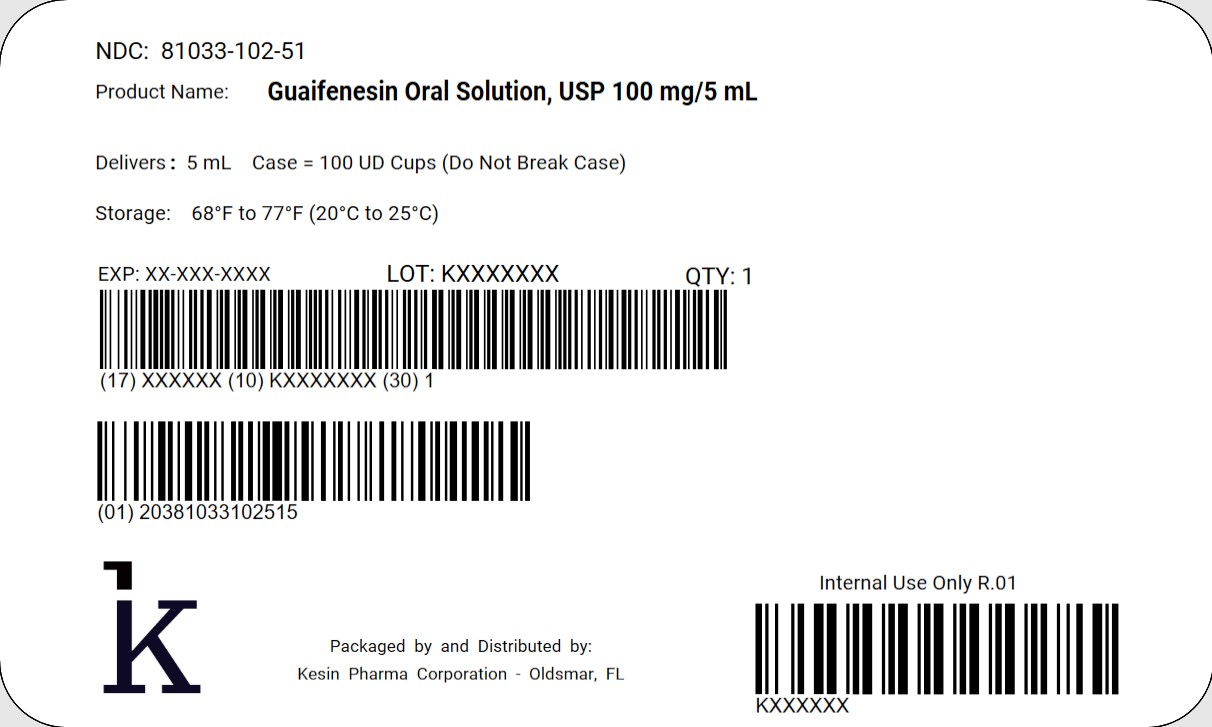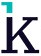 DRUG LABEL: Guaifenesin
NDC: 81033-102 | Form: LIQUID
Manufacturer: KESIN PHARMA CORPORATION
Category: otc | Type: HUMAN OTC DRUG LABEL
Date: 20250328

ACTIVE INGREDIENTS: GUAIFENESIN 100 mg/5 mL
INACTIVE INGREDIENTS: CITRIC ACID MONOHYDRATE; METHYLPARABEN; AMMONIUM GLYCYRRHIZATE; POTASSIUM CITRATE ANHYDROUS; PROPYLENE GLYCOL; PROPYLPARABEN; WATER; SORBITOL; SUCRALOSE

Guaifenesin Oral Solution, USP

Guaifenesin Solution 5mL

Expectorant
Sugar Free / Dye Free / Alcohol Free

Description

Each 5mL (1 teaspoonful) contains: Guaifenesin 100mg

Inactive Ingredients

Mixture of Guaifenesin with GRAS material additions including Citric Acid, Grape Flavor Methylparaben, Monoammonium Glycyrrhizate, Potassium Citrate, Propylene Glycol, Propylparaben, Purified Water, Sorbitol, Sucralose

Uses

Helps loosen phlegm (mucus) and thin bronchial secretions to make coughs more productive.

Warnings

Ask a doctor before us if you have
• cough that occurs with too much phlegm (mucus)
• cough that lasts or is chronic such as occurs with smoking, asthma, chronic bronchitis, or emphysema

Stop and ask a doctor if
• cough lasts mor than 7 days, comes back, or is accompanied by fever, rash, or persistent headache. These could be signs of a serious condition.
• you are hypersensitive to any of the ingredients

If pregnant or breast-feeding, ask a health professional before use.

Keep out of reach of children. In case of overdose, get medical help or contact a Poison Control Center right away.

Professional Note: Guaifenesin has been shown to produce a color interference with certain clinical laboratory determinations of 5-hydroxyindoleacetic acid (5-HIAA) and vanillylmandelic acid (VMA).

Directions

Follow dosage below or use as directed by a physician.
• Do not take more than 6 doses in any 24-hour period

Age | Dose
Adults and children 12 years and over | 10 to 20mL (2 to 4 teaspoonfuls) every 4 hours
Children 6 years to under 12 years | 5 to 10mL (1 to 2 teaspoonfuls) every 4 hours
Children 2 to under 6 years of age | 2.5 to 5mL (1/2 to 1 teaspoonful) every 4 hours
Children under 2 years of age | Consult a physician

How Supplied:

Guaifenesin Oral Solution is a clear, colorless solution with a grape flavor, free of visible foreign matter supplied in the following oral dosage forms:

NDC 81033-102-05: 5mL unit dose cup
NDC 81033-102-51: Case containing 100 unit dose cups of 5 mL packaged in 2 cartons of 50 unit dose cups each
NDC 81033-102-10: 10mL unit dose cup
NDC 81033-102-52: Case containing 100 unit dose cups of 10 mL packaged in 2 cartons of 50 unit dose cups each
NDC 81033-102-15: 15 mL unit dose cup
NDC 81033-102-53: Case containing 100 unit dose cups of 15 mL packaged in 2 cartons of 50 unit dose cups each

STORAGE

Keep tightly closed. Store at controlled room temperature, 20°C to 25°C (68°F to 77°F). [See USP]
Protect from light

QUESTIONS OR COMMENTS

Call 1-833-537-4679

Packaged by:
Kesin Pharma
Oldsmar, FL 34677
Effective: 09/2024

Rev. 03

5 mL Unit Dose Cup Case Label

NDC 81033-102-51

Guaifenesin Oral Solution, USP100 mg/5 mL

Delivers 5 mL

Case = 100 UD Cups (Do Not Break Case)

Store at 68°F to 77°F (20°C to 25°C)

QTY 1

10 mL Unit Dose Cup Case Label

NDC 81033-102-52

Guaifenesin Oral Solution, USP 200 mg/10 mL

Delivers 10 mL

Case = 100 UD Cups (Do Not Break Case)

Store at 68°F to 77°F (20°C to 25°C)

QTY 1

15 mL Unit Dose Cup Case Label

NDC 81033-102-53

Guaifenesin Oral Solution, USP 300 mg/15 mL

Delivers 15 mL

Case = 100 UD Cups (Do Not Break Case)

QTY 1